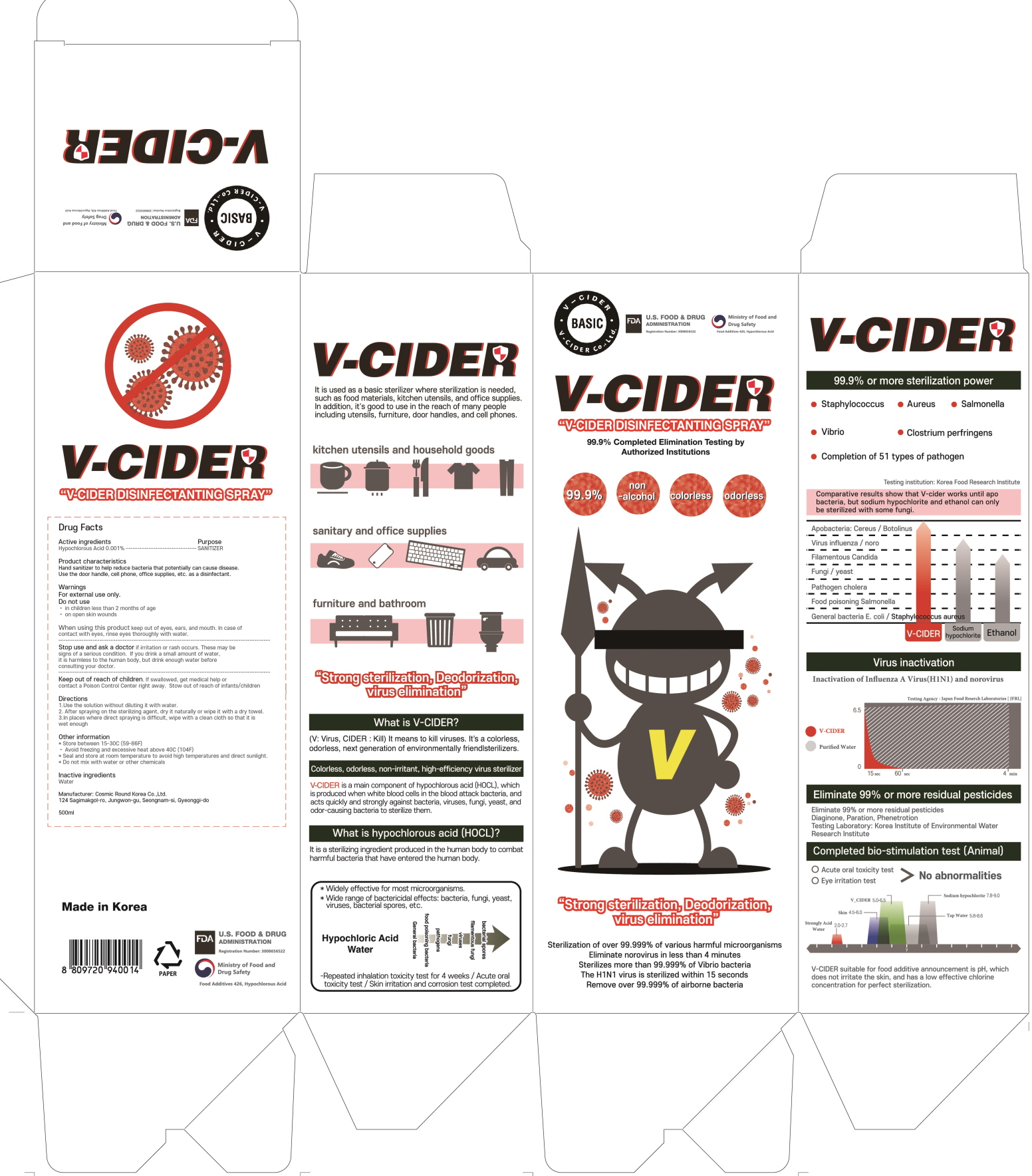 DRUG LABEL: V CIDER
NDC: 75392-010 | Form: LIQUID
Manufacturer: Cosmic Round Korea Co.,Ltd.
Category: otc | Type: HUMAN OTC DRUG LABEL
Date: 20200419

ACTIVE INGREDIENTS: Hypochlorous Acid 0.005 g/500 mL
INACTIVE INGREDIENTS: Water

ACTIVE INGREDIENT

Active ingredients: Hypochlorous Acid 0.001%

INACTIVE INGREDIENT

Inactive ingredients:

Water

PURPOSE

Purpose: SANITIZER

WARNINGS

For external use only.
Do not use
• in children less than 2 months of age
• on open skin wounds
-------------------------------------------------------------------------------------------------------
When using this product keep out of eyes, ears, and mouth. In case of contact with eyes, rinse eyes thoroughly with water.
--------------------------------------------------------------------------------------------------------
Stop use and ask a doctor if irritation or rash occurs. These may be signs of a serious condition. If you drink a small amount of water, it is harmless to the human body, but drink enough water before consulting your doctor.

Keep out of reach of children. If swallowed, get medical help or contact a Poison Control Center right away. Stow out of reach of infants/children.

Uses

Hand sanitizer to help reduce bacteria that potentially can cause disease.
Use the door handle, cell phone, office supplies, etc. as a disinfectant.

Directions

1.Use the solution without diluting it with water.
2. After spraying on the sterilizing agent, dry it naturally or wipe it with a dry towel.
3.In places where direct spraying is difficult, wipe with a clean cloth so that it is wet enough

Other information

* Store between 15-30C (59-86F)
• Avoid freezing and excessive heat above 40C (104F)
* Seal and store at room temperature to avoid high temperatures and direct sunlight.
* Do not mix with water or other chemicals.